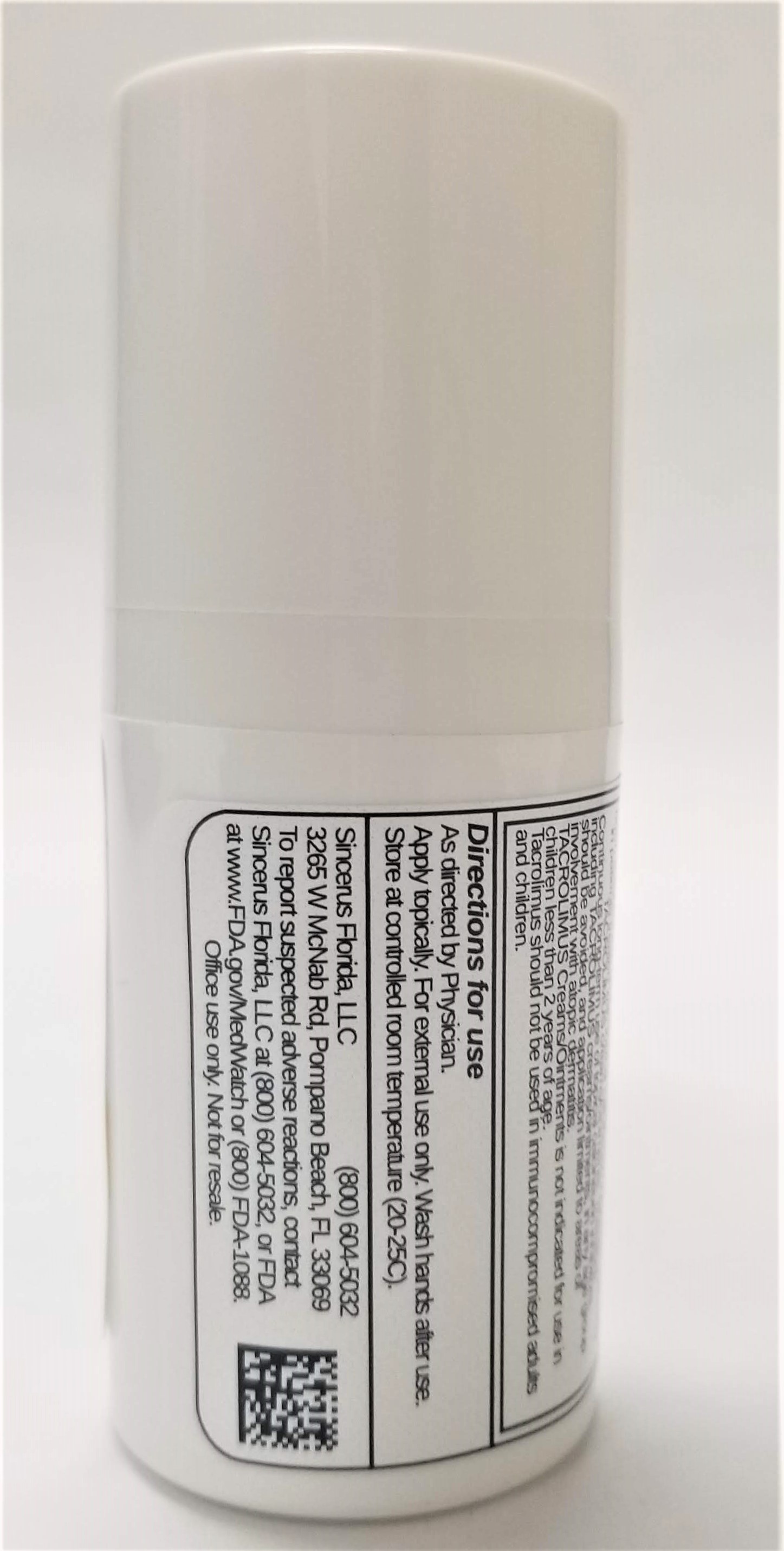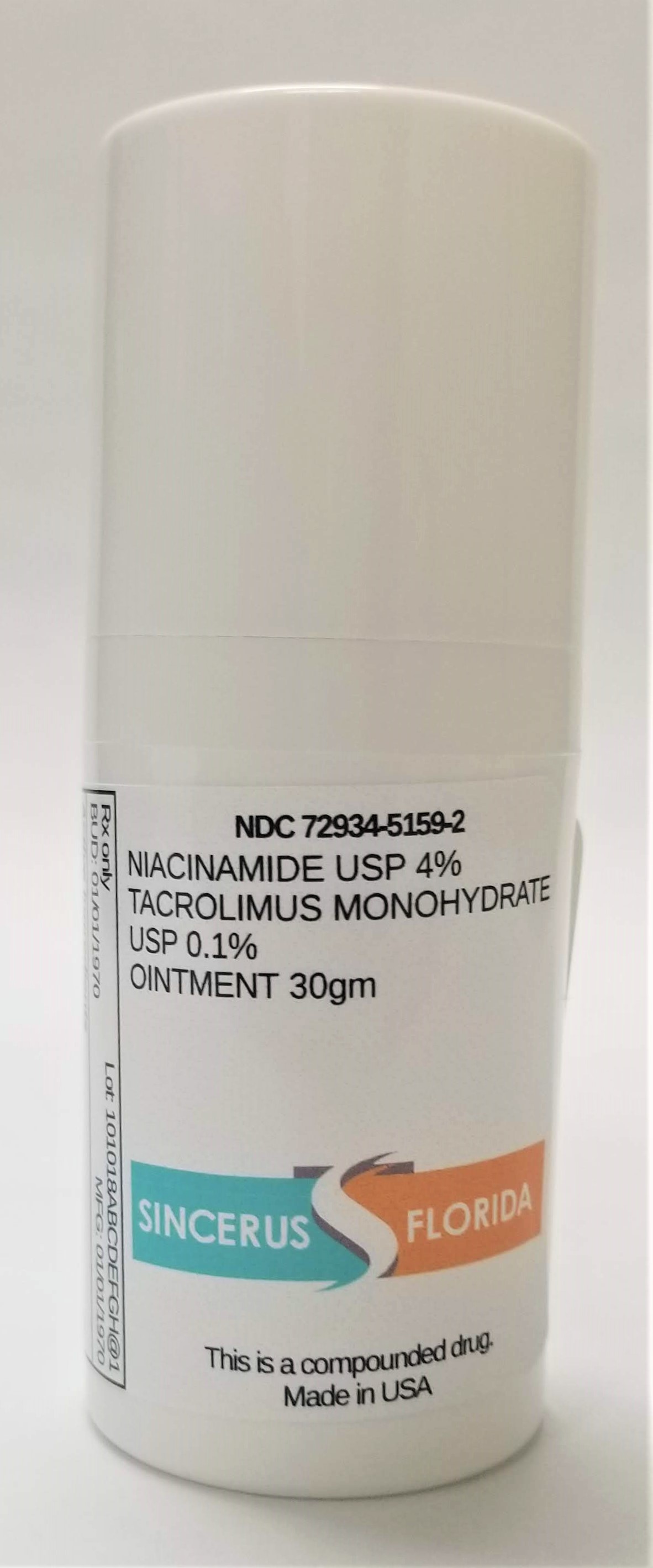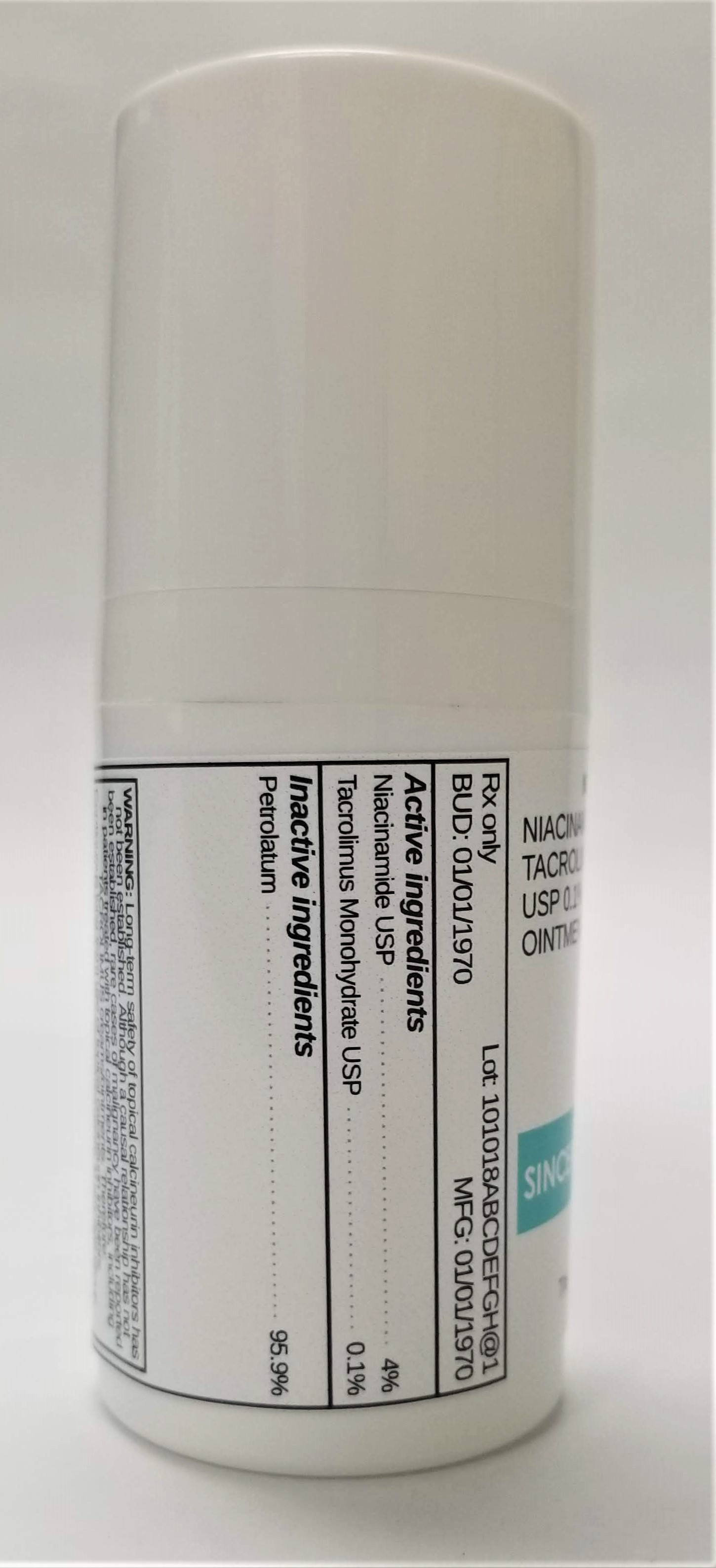 DRUG LABEL: NIACINAMIDE 4% / TACROLIMUS 0.1%
NDC: 72934-5159 | Form: OINTMENT
Manufacturer: Sincerus Florida, LLC
Category: prescription | Type: HUMAN PRESCRIPTION DRUG LABEL
Date: 20190424

ACTIVE INGREDIENTS: TACROLIMUS 0.1 g/100 g; NIACINAMIDE 4 g/100 g

NIACINAMIDE 4% / TACROLIMUS 0.1%